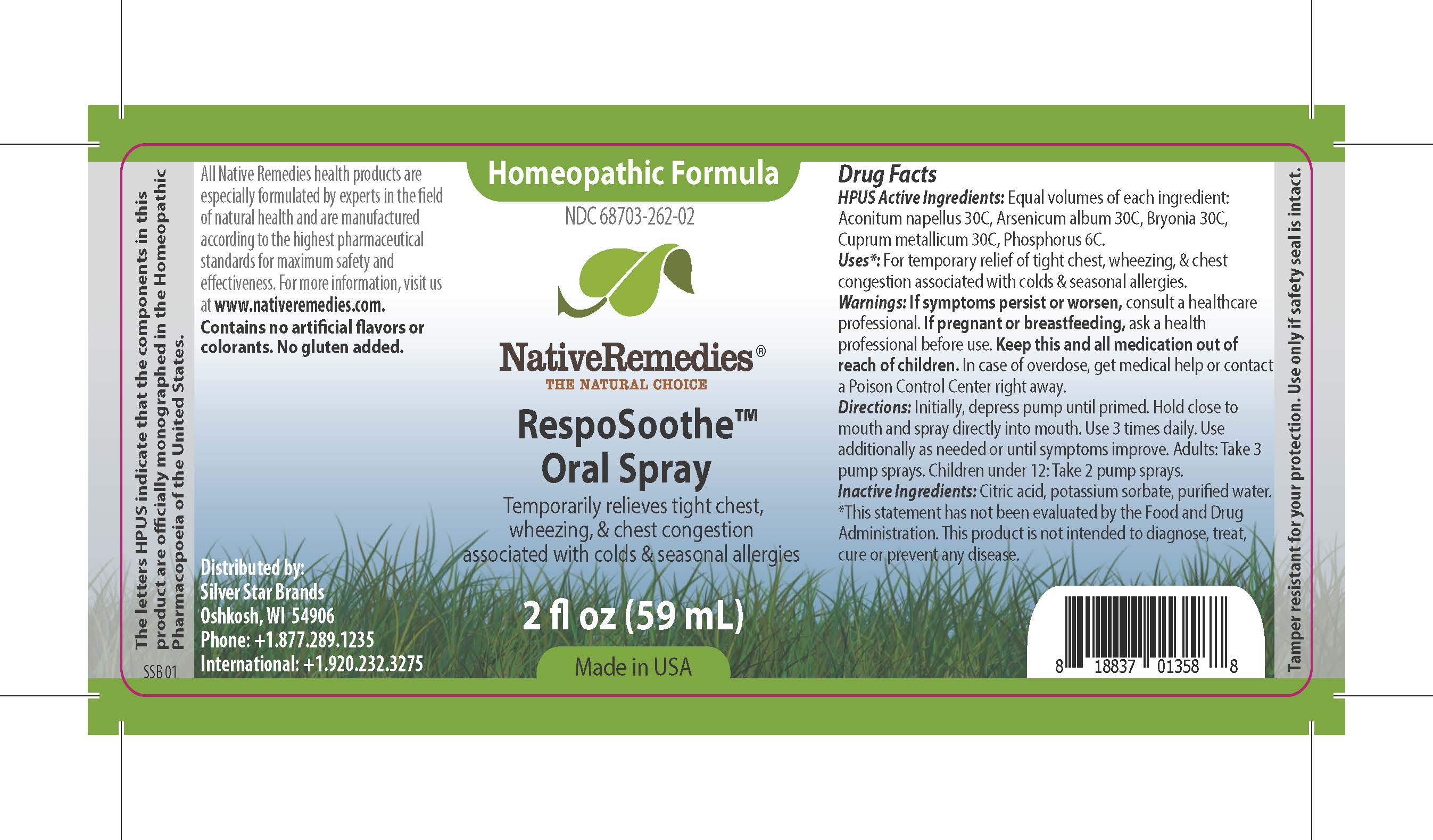 DRUG LABEL: RespoSoothe
NDC: 68703-262 | Form: SPRAY
Manufacturer: Silver Star Brands
Category: homeopathic | Type: HUMAN OTC DRUG LABEL
Date: 20161018

ACTIVE INGREDIENTS: ACONITUM NAPELLUS 30 [hp_C]/59 mL; ARSENIC TRIOXIDE 30 [hp_C]/59 mL; PHOSPHORUS 6 [hp_C]/59 mL; COPPER 30 [hp_C]/59 mL; BRYONIA ALBA ROOT 30 [hp_C]/59 mL
INACTIVE INGREDIENTS: ANHYDROUS CITRIC ACID; POTASSIUM SORBATE; WATER

NativeRemedies® RespoSoothe™ Oral Spray

HPUS Active Ingredients:

Equal volumes of each ingredient: Aconitum napellus 30C, Arsenicum album 30C, Bryonia 30C, Cuprum metallicum 30C, Phosphorus 6C.

Uses*:

For temporary relief of tight chest, wheezing, & chest congestion associated with colds & seasonal allergies.

*This statement has not been evaluated by the Food and Drug Administration. This product is not intended to diagnose, treat, cure or prevent any disease.

Warnings:

If symptoms persist or worsen, consult a healthcare professional. If pregnant or breastfeeding, ask a health professional before use. Keep this and all medication out of reach of children. In case of overdose, get medical help or contact a Poison Control Center right away.

Directions:

Initially, depress pump until primed. Hold close to mouth and spray directly into mouth. Use 3 times daily. Use additionally as needed or until symptoms improve. Adults: Take 3 pump sprays. Children under 12: Take 2 pump sprays.

OTHER SAFETY INFORMATION

All Native Remedies health products are especially formulated by experts in the field of natural health and are manufactured according to the highest pharmaceutical standards for maximum safety and effectiveness. For mroe information, visit us at www.nativeremedies.com.

Contains no artificial flavors or colorants. No gluten added.

Inactive Ingredients:

Citric acid, potassium sorbate, purified water.

KEEP OUT OF REACH OF CHILDREN

Keep this and all medication out of reach of children. In case of overdose, get medical help or contact a Poison Control Center right away.

PREGNANCY OR BREAST FEEDING

If pregnant or breastfeeding, ask a health professional before use.

PURPOSE

Temporarily relieves tight chest, wheezing, & chest congestion associated with colds & seasonal allergies